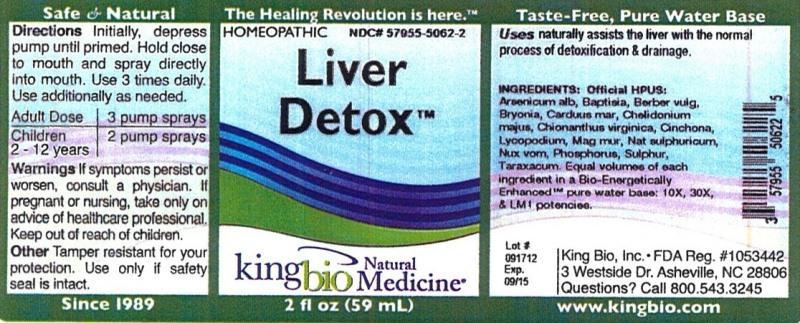 DRUG LABEL: Liver Detox
NDC: 57955-5062 | Form: LIQUID
Manufacturer: King Bio Inc.
Category: homeopathic | Type: HUMAN OTC DRUG LABEL
Date: 20121016

ACTIVE INGREDIENTS: ARSENIC TRIOXIDE 10 [hp_X]/59 mL; BAPTISIA TINCTORIA ROOT 10 [hp_X]/59 mL; BERBERIS VULGARIS ROOT BARK 10 [hp_X]/59 mL; BRYONIA ALBA ROOT 10 [hp_X]/59 mL; SILYBUM MARIANUM SEED 10 [hp_X]/59 mL; CHELIDONIUM MAJUS 10 [hp_X]/59 mL; CHIONANTHUS VIRGINICUS BARK 10 [hp_X]/59 mL; CINCHONA OFFICINALIS BARK 10 [hp_X]/59 mL; LYCOPODIUM CLAVATUM SPORE 10 [hp_X]/59 mL; MANGANESE CHLORIDE 10 [hp_X]/59 mL; SODIUM SULFATE 10 [hp_X]/59 mL; STRYCHNOS NUX-VOMICA SEED 10 [hp_X]/59 mL; PHOSPHORUS 10 [hp_X]/59 mL; SULFUR 10 [hp_X]/59 mL; TARAXACUM OFFICINALE 10 [hp_X]/59 mL
INACTIVE INGREDIENTS: WATER

Liver Detox

Active Ingredients

Official HPUS: Arsenicum album, Baptisia tinctoria, Berberis vulgaris, Bryonia, Carduus marianus, Chelidonium majus, Chionanthus virginica, Cinchona officinalis, Lycopodium clavatum, Manganum muriaticum, Natrum sulphuricum, Nux vomica, Phosphorus, Sulphur, Taraxacum officinale.

Inactive Ingredient

Equal volumes of each ingredient in a Bio-Energetically Enhanced pure water base: 10X, 30X and LM1 potencies.

Purpose

Uses naturally assists the liver with the normal process of detoxification and drainage.

Dosage and Administration

Directions Initially, depress pump until primed. Hold close to mouth and spray directly into mouth. Use 3 times daily. Use additionally as needed.

Adult Dose 3 pump sprays

Children 2-12 years 2 pump sprays

Warnings

If symptoms persist or worsen, consult a physician. If pregnant or nursing, take only on advice of healthcare professional. Keep out of reach of children.

Other: Tamper resistant for your protection. Use only if safety seal is intact.

Keep out of reach of children.

Indications and Usage

Uses naturally assists the liver with the normal process of detoxification and drainage.

PACKAGE LABEL

King Bio Inc.

3 Westside Dr.

Asheville, NC 28806

Questions? Call 800.543.3245

www.kingbio.com